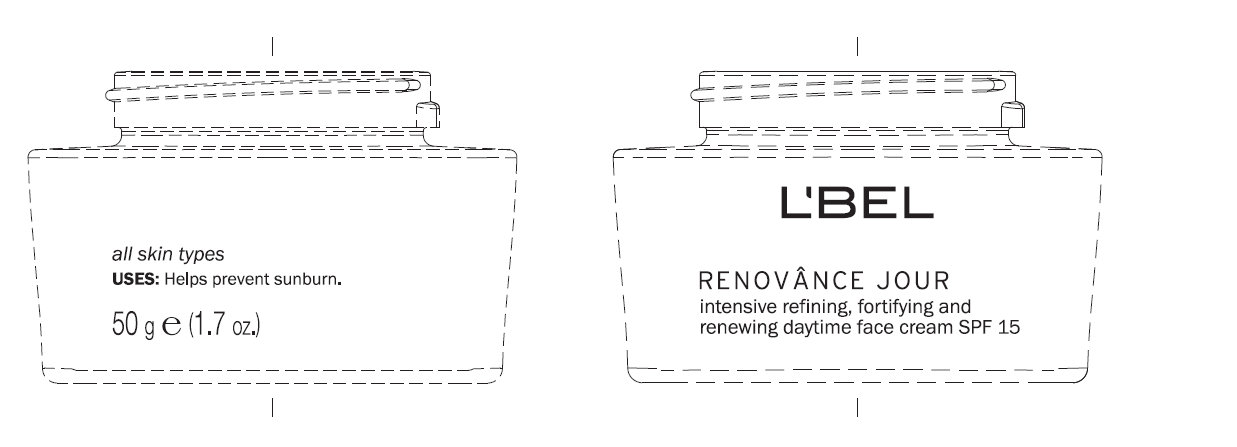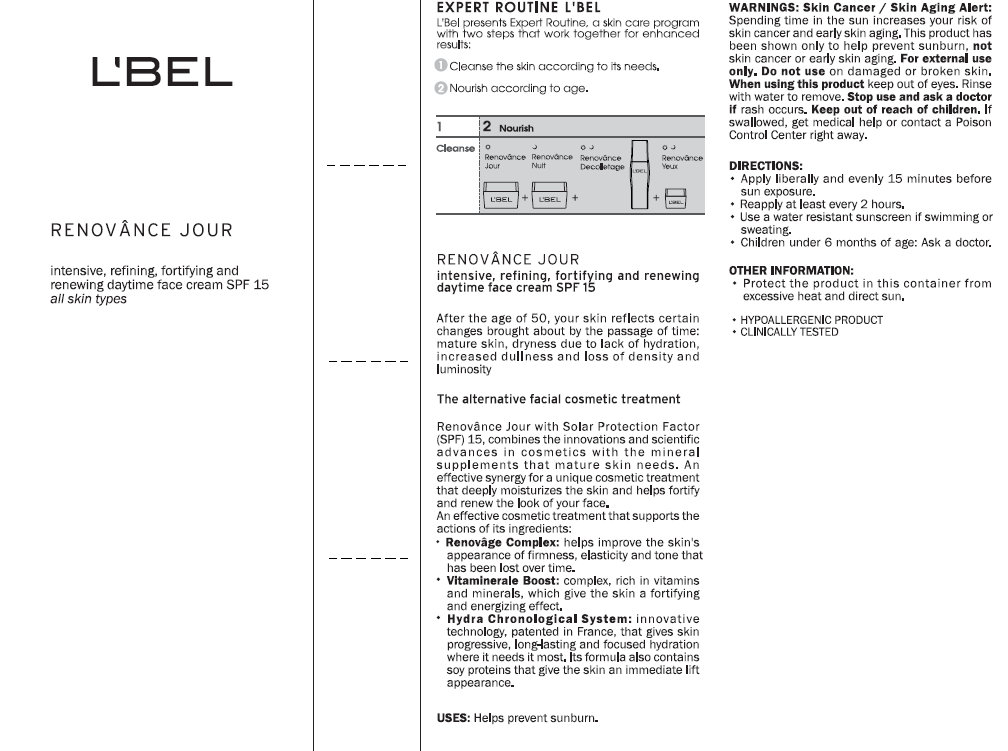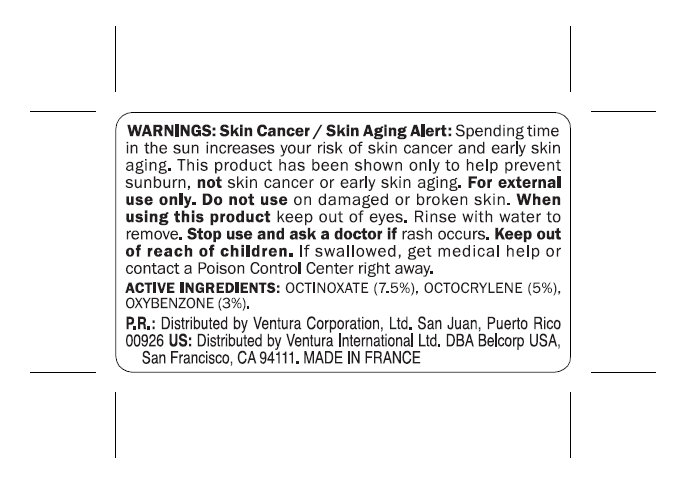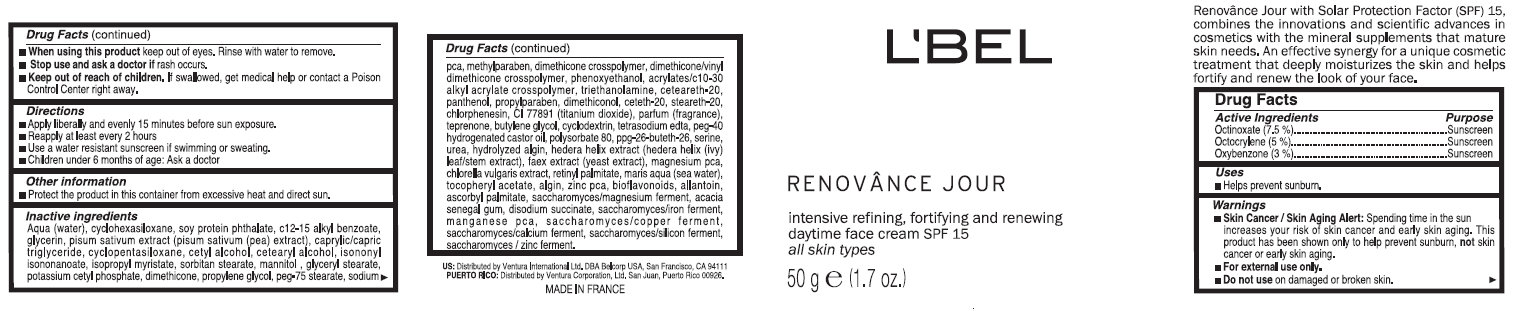 DRUG LABEL: LBEL RENOVANCE JOUR Daytime Face SPF 15 All Skin Types
NDC: 43596-0004 | Form: CREAM
Manufacturer: Ventura Corporation, LTD
Category: otc | Type: HUMAN OTC DRUG LABEL
Date: 20120329

ACTIVE INGREDIENTS: OCTINOXATE 7.5 g/100 g; OCTOCRYLENE 5 g/100 g; OXYBENZONE 3 g/100 g
INACTIVE INGREDIENTS: WATER; CYCLOMETHICONE 6; ALKYL (C12-15) BENZOATE; GLYCERIN; PEA; MEDIUM-CHAIN TRIGLYCERIDES; CYCLOMETHICONE 5; CETYL ALCOHOL; CETOSTEARYL ALCOHOL; ISONONYL ISONONANOATE; ISOPROPYL MYRISTATE; SORBITAN MONOSTEARATE; MANNITOL; GLYCERYL MONOSTEARATE; POTASSIUM CETYL PHOSPHATE; DIMETHICONE; PROPYLENE GLYCOL; PEG-75 STEARATE; SODIUM PYRROLIDONE CARBOXYLATE; METHYLPARABEN; PHENOXYETHANOL; CARBOMER INTERPOLYMER TYPE A (55000 MPA.S); TROLAMINE; POLYOXYL 20 CETOSTEARYL ETHER; PANTHENOL; PROPYLPARABEN; CETETH-20; STEARETH-20; CHLORPHENESIN; TITANIUM DIOXIDE; TEPRENONE; BUTYLENE GLYCOL; EDETATE SODIUM; POLYOXYL 40 HYDROGENATED CASTOR OIL; POLYSORBATE 80; SERINE; UREA; HEDERA HELIX LEAF; YEAST; CHLORELLA VULGARIS; VITAMIN A PALMITATE; .ALPHA.-TOCOPHEROL ACETATE; ZINC PIDOLATE; ALLANTOIN; ASCORBYL PALMITATE; ACACIA; SODIUM SUCCINATE ANHYDROUS

L'BEL RENOVANCE JOUR Daytime Face Cream SPF 15 All Skin Types

Active Ingredients

OCTINOXATE (7.5%)
OCTOCRYLENE (5.0%)
OXYBENZONE (3.0%)

Uses

- Helps prevent sunburn.

Warnings

- Skin Cancer / Skin Aging Alert: Spending time in the sun increases your risk of skin cancer and early skin aging. This product has been shown only to help prevent sunburn, not skin cancer or early skin aging.
- For external use only.

Do not use

on damaged or broken skin.

When using this product

keep out of eyes. Rinse with water to remove.

Stop use and ask a doctor if

rash occurs.

Keep out of reach of children.

If swallowed, get medical help or contact a Poison Control Center right away.

Directions

- Apply liberally and evenly 15 minutes before sun exposure.
- Reapply at least every 2 years
- Use a water resistant sunscreen if swimming or sweating.
- Children under 6 months of age: Ask a doctor.

Other Information

- Protect the product in this container from excessive heat and direct sun.

Inactive Ingredients

Aqua (water), cyclohexasiloxane, soy protein phthalate, c12-15 alkyl benzoate, glycerin, pisum sativum extract (pisum sativum (pea) extract), caprylic/capric triglyceride, cyclopentasiloxane, cetyl alcohol, cetearyl alcohol, isononyl isononanoate, isopropyl myristate, sorbitan stearate, mannitol , glyceryl stearate, potassium cetyl phosphate, dimethicone, propylene glycol, peg-75 stearate, sodium pca, methylparaben, dimethicone crosspolymer, dimethicone/vinyl dimethicone crosspolymer, phenoxyethanol, acrylates/c10-30 alkyl acrylate crosspolymer, triethanolamine, ceteareth-20, panthenol, propylparaben, dimethiconol, ceteth-20, steareth-20, chlorphenesin, ci 77891 (titanium dioxide), parfum (fragrance), teprenone, butylene glycol, cyclodextrin, tetrasodium edta, peg-40 hydrogenated castor oil, polysorbate 80, ppg-26-buteth-26, serine, urea, hydrolyzed algin, hedera helix extract (hedera helix (ivy) leaf/stem extract), faex extract (yeast extract), magnesium pca, chlorella vulgaris extract, retinyl palmitate, maris aqua (sea water), tocopheryl acetate, algin, zinc pca, bioflavonoids, allantoin, ascorbyl palmitate, saccharomyces/magnesium ferment, acacia senegal gum, disodium succinate, saccharomyces/iron ferment, manganese pca, saccharomyces/copper ferment, saccharomyces/calcium ferment, saccharomyces/silicon ferment, saccharomyces/zinc ferment.

Purpose

Sunscreen

EXPERT ROUTINE L'BEL

L'Bel presents Expert Routine, a skin care program with two steps that work together for enhanced results:
1. Cleanse the skin according to its needs.
2. Nourish according to the age.
RENOVANCE JOUR
intensive, refining, fortifying and renewing daytime face cream SPF 15
After the age of 50, your skin reflects certain changes brought about by the passage of time: increased dullness and loss of density and luminosity
The alternative facial cosmetic treatment
Renovance Jour with Solar Protection Factor (SPF) 15, combines the innovations and scientific advances in cosmetics with the mineral supplements that mature skin needs. An effective synergy for a unique cosmetic treatment that deeply moisturizes the skin and helps fortify and renew the look of your face.
An effective cosmetic treatment that supports the actions of its ingredients:

- Renovage Complex: helps improve the skin’s appearance of firmness, elasticity and tone that has been lost over time.
- Vitaminerale Boost: complex, rich in vitamins and minerals, which give the skin a fortifying and energizing effect.
- Hydra Chronological System: innovative technology, patented in France, that gives skin progressive, long-lasting and focused hydration where it needs it most. Its formula also contains soy proteins that give the skin an immediate lift appearance.

USES: Helps prevent sunburn.
WARNINGS: Skin Cancer / Skin Aging Alert: Spending time in the sun increases your risk of skin cancer and early skin aging. This product has been shown only to help prevent sunburn, not skin cancer or early skin aging. For external use only. Do not use on damaged or broken skin. When using this product keep out of eyes. Rinse with water to remove. Stop use and ask a doctor if rash occurs. Keep out of reach of children. If swallowed, get medical help or contact a Poison Control Center right away.
DIRECTIONS:

- Apply liberally and evenly 15 minutes before sun exposure.
- Reapply at least every 2 hours.
- Use a water resistant sunscreen if swimming or sweating.
- Children under 6 months of age: Ask a doctor.

OTHER INFORMATION:

- Protect the product in this container from excessive heat and direct sun.

- HYPOALLERGENIC PRODUCT
- CLINICALLY TESTED

PACKAGE LABEL

L'BEL RENOVANCE JOUR intensive refining, fortifying and renewing daytime face cream SPF 15 all skin types 50g e (1.7 oz.) Renovance Jour with Solar Protection Factor (SPF) 15, combines the innovations and scientific advances in cosmetics with the mineral supplements that mature skin needs. An effective synergy for unique cosmetic treatment that deeply moisturizes the skin and helps fortify and renew the look of your face.